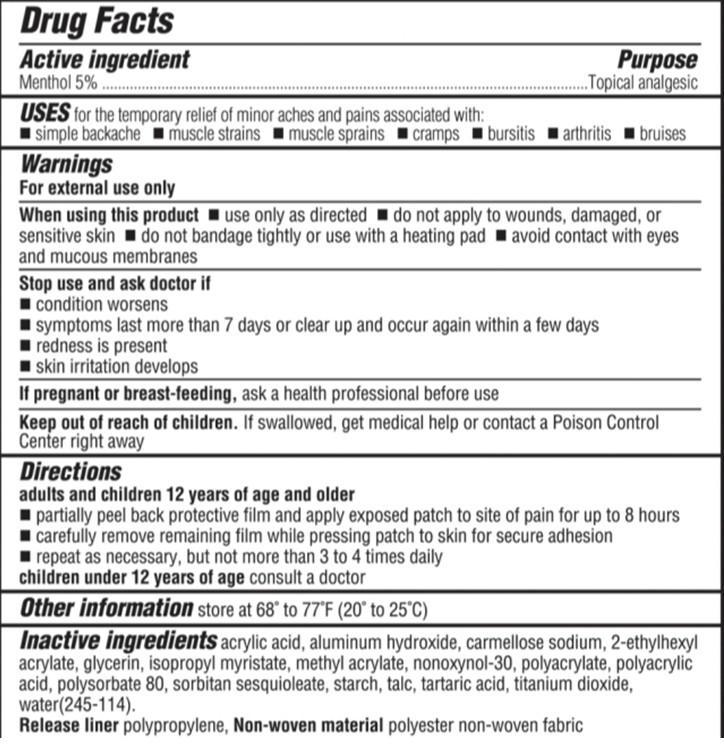 DRUG LABEL: cold  hot patch
NDC: 62379-001 | Form: PATCH
Manufacturer: Simple Diagnostics, Inc.
Category: otc | Type: HUMAN OTC DRUG LABEL
Date: 20150223

ACTIVE INGREDIENTS: MENTHOL 5 g/100 g
INACTIVE INGREDIENTS: ACRYLIC ACID; ALUMINUM HYDROXIDE; CROSCARMELLOSE SODIUM; 2-ETHYLHEXYL ACRYLATE; GLYCERIN; ISOPROPYL MYRISTATE; METHYL ACRYLATE; NONOXYNOL-30; SODIUM POLYACRYLATE (8000 MW); POLYACRYLIC ACID (8000 MW); POLYSORBATE 80; SORBITAN SESQUIOLEATE; STARCH, POTATO; TALC; TARTARIC ACID; TITANIUM DIOXIDE; WATER

cold & hot patch

Active Ingredient

Menthol 5.00%.

Purpose

Topical analgesic

Use

temporarily relieves minor aches and pains of muscles and joints due to
.arthritis .simple backache .strains . sprains
.bursitis .tendonitis . Bruises . Cramps

Warnning

For external use only.
When using this product.use only as directed . avoid contact with eyes and mucous membranes. do not apply to wounds or damaged skin.do not bandage tightly or use a heating pad
Stop use and ask doctor if
.excessive redness or irritation is present
.condition worsens
.pain persist for more than 7 days
.symptoms clear up and occur again within a few days
If pregnant or breast-feeding, ask a health professional before use, keep out of reach of childeren.If swallowed, get medical help or contact a poison control center right away.

KEEP OUT OF REACH OF CHILDREN

keep out of reach of childeren.If swallowed, get medical help or contact a poison control center right away.

Directions

.adults and children 12 years and over: apply patch to affected area as needed but not more than 4 times daily
.children under 12 years: ask a doctor
. for easy application: grasp both ends of pad firmly, pull at both ends. Stretch pad until the backing separates.
Remove protective film while applying pad directly to site of pain.

Inactive Ingredients

Acrylic Acid,Aluminum Hydroxide,Carmellose Sodium,2 Ethylhexyl Acrylate,Glycerin,Isopropyl Myristate,Methyl Acrylate,Nonoxynol 30,
Polyacrylate,Polyacrylic Acid,Polysorbate 80,Sorbitan Sesquioleate,Starch,Talc,Tartaric Acid,Titanium Dioxide,Water